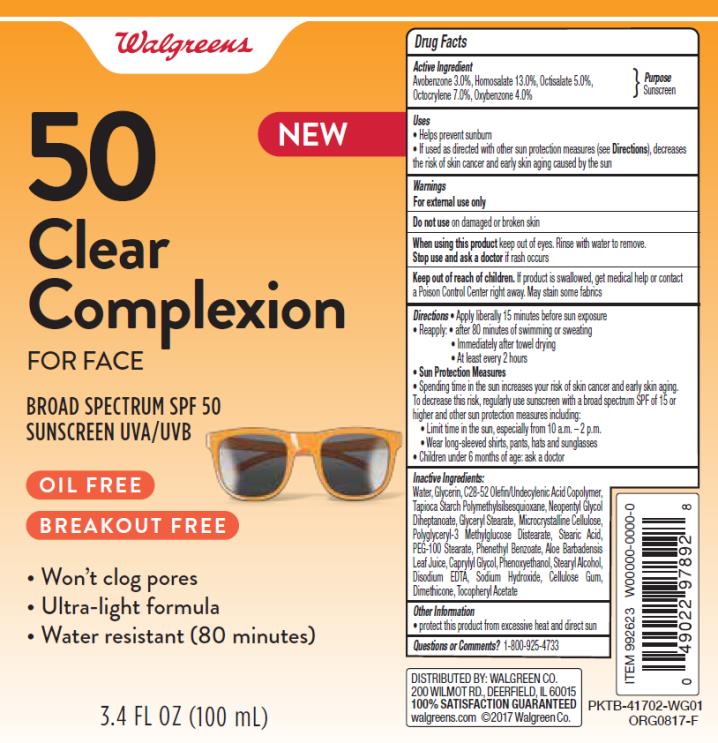 DRUG LABEL: Walgreen Clear Complexion
NDC: 0363-9923 | Form: LOTION
Manufacturer: Walgreen Company
Category: otc | Type: HUMAN OTC DRUG LABEL
Date: 20171005

ACTIVE INGREDIENTS: AVOBENZONE 3 g/100 g; HOMOSALATE 13 g/100 g; OCTOCRYLENE 7 g/100 g; OCTISALATE 5 g/100 g; OXYBENZONE 4 g/100 g
INACTIVE INGREDIENTS: WATER; GLYCERIN; NEOPENTYL GLYCOL DIHEPTANOATE; GLYCERYL MONOSTEARATE; MICROCRYSTALLINE CELLULOSE; STEARIC ACID; POLYOXYL 100 STEARATE; PHENETHYL BENZOATE; ALOE VERA LEAF; CAPRYLYL GLYCOL; PHENOXYETHANOL; STEARYL ALCOHOL; EDETATE DISODIUM ANHYDROUS; SODIUM HYDROXIDE; CARBOXYMETHYLCELLULOSE SODIUM; DIMETHICONE; ALPHA-TOCOPHEROL ACETATE

WAG Sun Clear Face Lot SPF50 34oz

1491-05 Rev 02

Walgreens Clear Complexion

Active Ingredients

Avobenzone 3%, Homosalate 13%, Octocrylene 7%, Octisalate 5%, Oxybenzone 4%

Purpose

Sunscreen

Uses

- helps prevent sunburn
- if used as directed with other sun protection measures (see Directions), decreases the risk of skin cancer and early skin aging caused by the sun

Warnings

For external use only

Do not use

on damaged or broken skin

When using this product

keep out of eyes. Rinse with water to remove.

Stop use and ask a doctor

if rash occurs

Keep out of reach of children.

If swallowed, get medical help or contact a Poison Control Center right away.

Directions

- apply liberally 15 minutes before sun exposure
- reapply:
  • after 80 minutes of swimming or sweating
  • immediately after towel drying
  • at least every 2 hours
- Sun Protection Measures. Spending time in the sun increases your risk of skin cancer and early skin aging. To decrease this risk, regularly use a sunscreen with a Broad Spectrum SPF of 15 or higher and other sun protection measures including:
  • limit time in the sun, especially from 10 a.m. - 2 p.m.
  • wear long-sleeve shirts, pants, hats, and sunglasses
- children under 6 months: Ask a doctor

Inactive Ingredients

Water, Glycerin, C28-52 Olefin/Undecylenic Acid Copolymer, Tapioca Starch Polymethylsilsesquioxane, Neopentyl Glycol Diheptanoate, Glyceryl Stearate, Microcrystalline Cellulose, Polyglyceryl-3 Methylglucose Distearate, Stearic Acid, PEG 100 Stearate, Phenethyl Benzoate, Aloe Barbadensis Leaf Juice, Caprylyl Glycol, Phenoxyethanol, Stearyl Alcohol, Disodium EDTA, Sodium Hydroxide, Cellulose Gum, Dimethicone, Tocopherol Acetate

Other Information

- for use on skin only. Avoid contact with fabric
- protect this product from excessive heat and direct sun

Questions or comments?

www.walgreens.com or call toll free 1-800-XXX-XXXX

PRINCIPAL DISPLAY PANEL

50
Clear
Complexion
FOR FACE
SPF 50
Sunscreen UVA/UVB
3.4 FL OZ (100 mL)